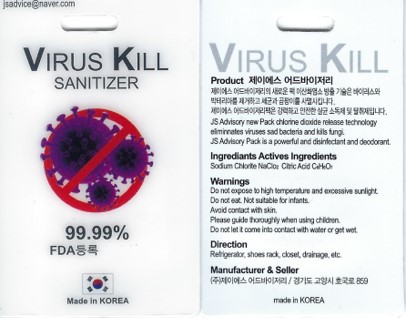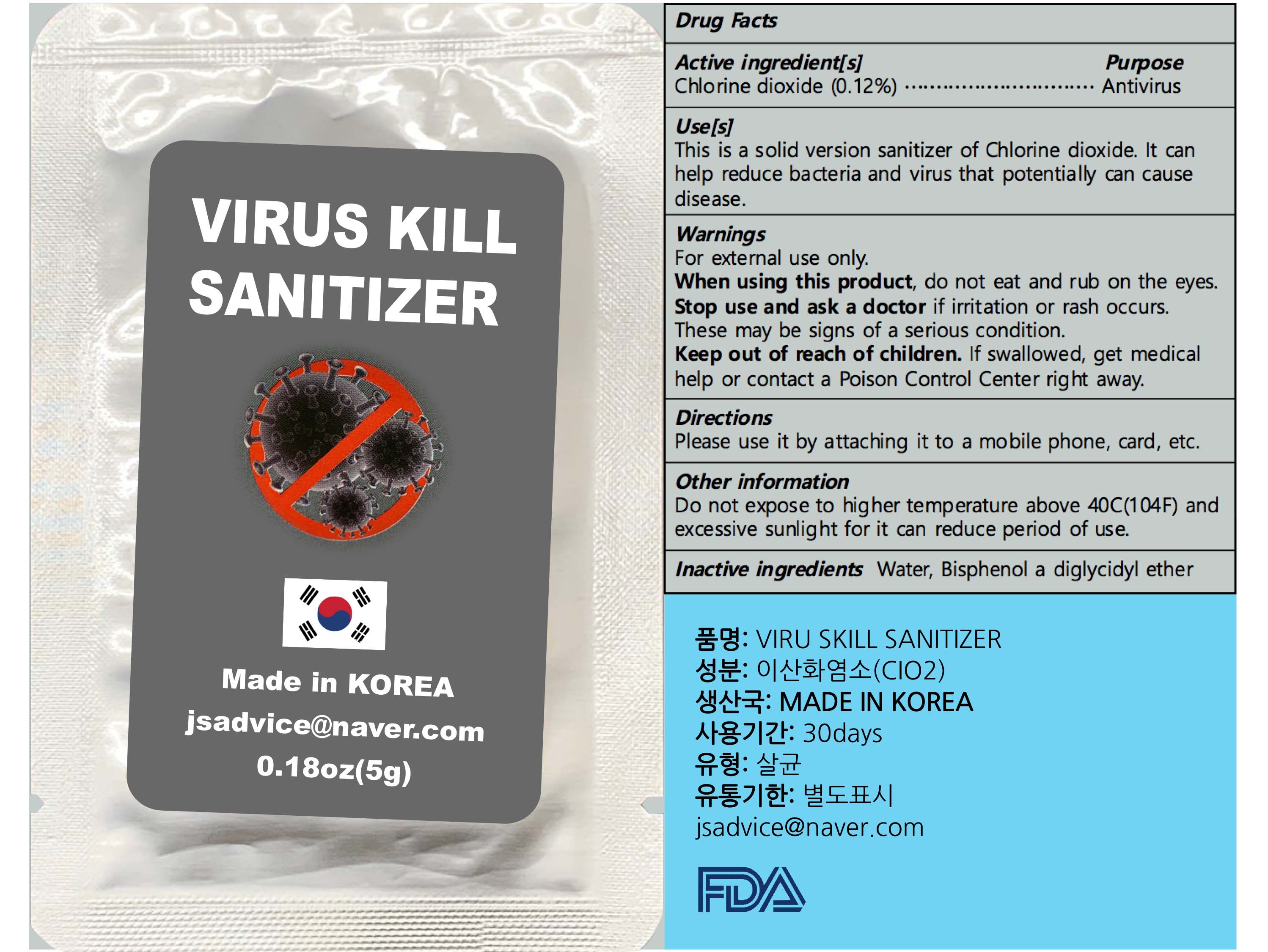 DRUG LABEL: VIRUS KILL SANITIZER
NDC: 81258-202 | Form: STICK
Manufacturer: JS Advisory Co., Ltd
Category: otc | Type: HUMAN OTC DRUG LABEL
Date: 20221108

ACTIVE INGREDIENTS: CHLORINE DIOXIDE 0.12 g/100 g
INACTIVE INGREDIENTS: BISPHENOL A DIGLYCIDYL ETHER; WATER

Active ingredient[s]

Chlorine dioxide (0.12%)

Purpose

Antivirus

Use[s]

This is a solid version sanitizer of Chlorine dioxide. It can help reduce bacteria and virus that potentially can cause disease.

Warnings

For external use only.

When using this product

do not eat and rub on the eyes.

Stop use and ask a doctor

if irritation or rash occurs.

These may be signs of a serious condition.

Keep out of reach of children.

If swallowed, get medical help or contact a Poison Control Center right away.

Directions

Please use it by attaching it to a mobile phone, card, etc.

Other information

Do not expose to higher temperature above 40C(104F) and excessive sunlight for it can reduce period of use.

Inactive ingredients

Water, Bisphenol a diglycidyl ether